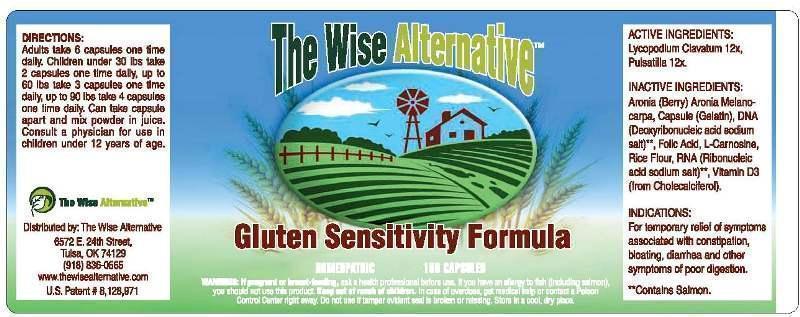 DRUG LABEL: Gluten Sensitivity Formula
NDC: 51096-0001 | Form: CAPSULE
Manufacturer: The Wise Alternative
Category: homeopathic | Type: HUMAN OTC DRUG LABEL
Date: 20130305

ACTIVE INGREDIENTS: LYCOPODIUM CLAVATUM SPORE 12 [hp_X]/1 mg; PULSATILLA VULGARIS 12 [hp_X]/1 mg
INACTIVE INGREDIENTS: ARONIA MELANOCARPA FRUIT; GELATIN; ONCORHYNCHUS MASOU SPERM DNA; FOLIC ACID; CARNOSINE; BROWN RICE; CYBERLINDNERA JADINII RNA; CHOLECALCIFEROL

Drug Facts

ACTIVE INGREDIENTS

Lycopodium Clavatum 12X, Pulsatilla 12X

INDICATIONS

For temporary relief of symptoms associated with constipation, bloating, diarrhea and othe symptoms of poor digetsion.

WARNINGS

If pregnant or breastfeeding, ask a health professional before use. If you have allergy to fish (including Salmon), you should not use this product. Keep out of reach of children. In case of overdose, get medical help or contact a Poison Control Center right away. Do not use if tamper evident seal is borken or missing. Store in a cool, dry place.

DIRECTIONS

Adults take 6 capsules one time daily. Children under 30 lbs take 2 capsules one time daily, up to 60 lbs take 3 capsules one time daily, up to 90 lbs take 4 capsules one time daily. Can take capsule apart and mix powder in juice. Consult a physician for ude in children under 12 years of age.

INACTIVE INGREDIENTS

Aronia (berry), Capsule (Gelatin), DNA (Deoxyribonucleic acidum sodium salt), Folic Acid, L-Carnosine, Rice Flour, RNA (Ribonucleic acid sodium salt), Vitamin D3 (from Cholecalciferol)

KEEP OUT OF REACH OF CHILDREN

In case of overdose, get medical help or contact a Poison Control Center right away.

INDICATIONS AND USAGE

For temporary relief of symptoms associated with constipation, bloating, diarrhea and othe symptoms of poor digetsion.

QUESTIONS

Distributed by: The Wise Alternative

6572 E. 24th Street

Tulsa, OK 74129

(918) 896-0665

www.thewisealternative.com

PACKAGE LABEL

The Wise Alternative

Gluten Sensitivity Formula

Homeopathic 180 Capsules